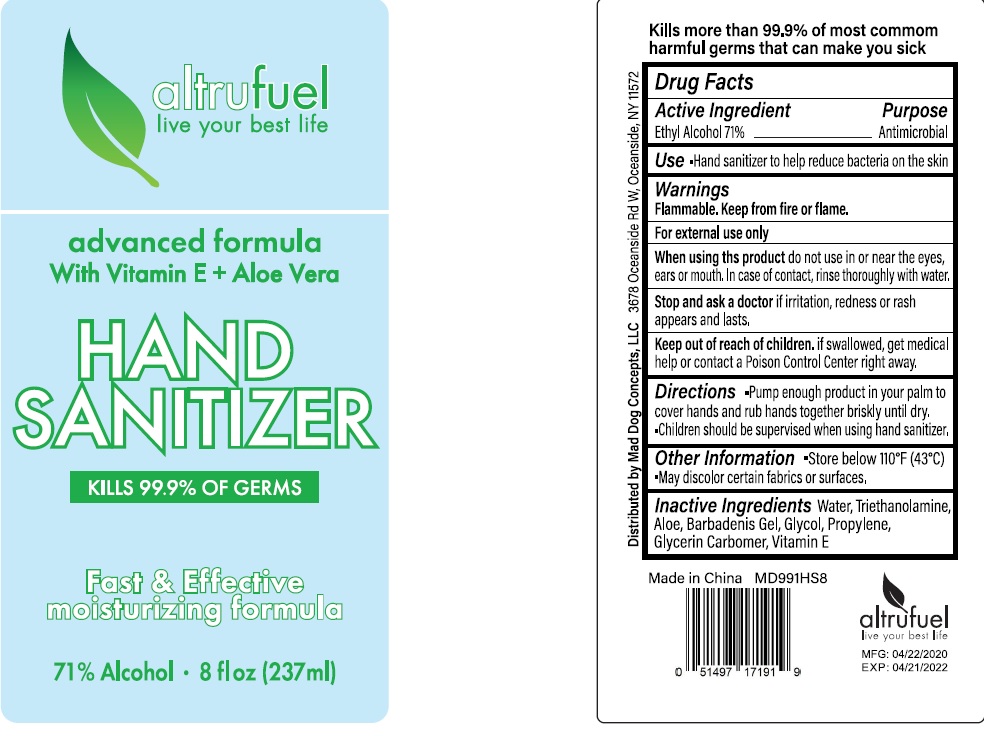 DRUG LABEL: altrufuel Hand Sanitizer With Vitamin E and Aloe Vera Moisturizing Formula
NDC: 75780-002 | Form: GEL
Manufacturer: NINGBO MEINEKE Biotech Technology Co., Ltd.
Category: otc | Type: HUMAN OTC DRUG LABEL
Date: 20200522

ACTIVE INGREDIENTS: alcohol 71 mL/100 mL
INACTIVE INGREDIENTS: WATER; PROPYLENE GLYCOL; ALOE VERA LEAF; CARBOMER 934; GLYCERIN

Drug facts

Active ingredient Purpose

Ethyl Alcohol 71% ... Antimicrobial

PURPOSE

Hand sanitizer to help decrease bacteria on the skin.

Children should be supervised when using hand sanitizer.

INDICATIONS AND USAGE

keep out of eyes

when water, soap and towel are not available

WARNINGS

For external use only.
Flammable. Keep away from fire or flame.

When using this products, do not use in or near the eyes, ears or mouth. In case of contact, rinse thoroghly with water

Stop using and ask a doctor, if redness and irritation appears and lasts.

Other information:

Store below 110℉（43℃）

May discolor certain fabrics or surfaces.

DOSAGE AND ADMINISTRATION

Pump enough products in your palms to cover hands and rub together briskly until dry.

Children must be supervised in using hand sanitizer

INACTIVE INGREDIENT

Water, Triethanolamine, Aloe, Barbadenis Gel, Glycol, Propylene, Glycerin Carbomer, Vitamin E